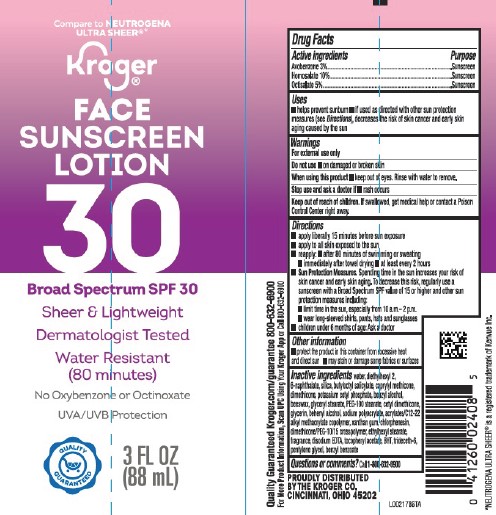 DRUG LABEL: Avobenzone, Homosalate, Octisalate
NDC: 59450-932 | Form: LOTION
Manufacturer: The Kroger Co.
Category: otc | Type: HUMAN OTC DRUG LABEL
Date: 20260227

ACTIVE INGREDIENTS: AVOBENZONE 30 mg/1 mL; HOMOSALATE 100 mg/1 mL; OCTISALATE 50 mg/1 mL
INACTIVE INGREDIENTS: WATER; DIETHYLHEXYL 2,6-NAPHTHALATE; SILICON DIOXIDE; BUTYLOCTYL SALICYLATE; CAPRYLYL TRISILOXANE; DIMETHICONE; POTASSIUM CETYL PHOSPHATE; BENZYL ALCOHOL; YELLOW WAX; GLYCERYL MONOSTEARATE; PEG-100 STEARATE; CETYL DIMETHICONE 150; GLYCERIN; DOCOSANOL; SODIUM POLYACRYLATE (8000 MW); BUTYL ACRYLATE/C16-C20 ALKYL METHACRYLATE/METHACRYLIC ACID/METHYL METHACRYLATE COPOLYMER; XANTHAN GUM; CHLORPHENESIN; DIMETHICONE/PEG-10/15 CROSSPOLYMER; ETHYLHEXYL STEARATE; EDETATE DISODIUM ANHYDROUS; .ALPHA.-TOCOPHEROL ACETATE; BUTYLATED HYDROXYTOLUENE; TRIDECETH-6; PENTYLENE GLYCOL; BENZYL BENZOATE

Kroger D32.000/D32AA
Sheer Touch Sunscreen SPF 30

Active Ingredients

Avobenzone 3%

Homosalate 10%

Octisalate 5%

Purpose

Sunscreen

Uses

- helps prevent sunburn
- if used as directed with other sun protection measures (See Directions), decreases the risk of skin cancer and early skin aging caused by the sun

Warnings

For external use only

Do not use

- on damaged or broken skin

When using this product

- keep out of eyes. Rinse with water to remove.

Stop use and ask a doctor if

- rash occurs

Keep out of reach of children.

If swallowed, get medical help or contact a Poison Control right away.

Directions

- apply liberaly 15 minutes before sun exposure
- apply to all skin exposed to the sun
- reapply:
- after 80 minutes of swimming or sweating
- immediately after towel drying
- at least every 2 hours
- Sun Protection Measures. Spending time in the sun increases your risk of skin cancer and early skin aging. To decrease this risk, regularly use a sunscreen with Broad Spectrum SPF value of 15 or higher and other sun protection measures including:
- limit time in the sun, especialy from 10 a.m.-2 p.m.
- wear long-sleeved shirts, pants, hats and sunglasses
- children under 6 months of age: Ask a doctor

Other information

- protect the product in this container from excessive heat and direct sun
- may stain or damage some fabrics or surfaces

Inactive ingredients

water, diethylhexyl 2, 6-naphthalate, silica, butyloctyl salicylate, caprylyl methicone, dimethicone, potassium cetyl phosphate, benzyl alcohol, beeswax, glyceryl stearate, PEG-100 stearate, cetyl dimethicone, glycerin, behenyl alcohol, sodium polyacrylate, acrylates/C12-22 alkyl methacrylate copolymer, xanthan gum, chlorphenesin, dimethicone/PEG-10/15 crosspolymer, ethylhexyl stearate, fragrance, disodium EDTA, tocopheryl acetate, BHT, trideceth-6, pentylene glycol, benzyl benzoate

Questions or comments?

Call 1-800-632-6900

Adverse Reactions

PROUDLY DISTRIBUTED BY THE KROGER CO.

CINCINNATI, OHIO 45202

Quality Guaranteed Kroger.com/guarantee 800-632-6900

For More Product Information, Scan UPC Using Your Kroger App or Call 800-632-6900

Disclaimer

*NEUTROGENA ULTRA SHEER®is a registered trademark of Kenvue Inc.

Principal Display Panel

Compare to NEUTROGENA ULTRA SHEER®*

Kroger®

FACE SUNSCREEN LOTION 30

Broad Spectrum SPF 30

Sheer & Lightweight

Dermatologist Tested

Water Resistant (80 minutes)

No Oxybenzone or Octinoxate

UVA/UVB Protection

QUALITY GUARANTEED

3 FL OZ (88 mL)